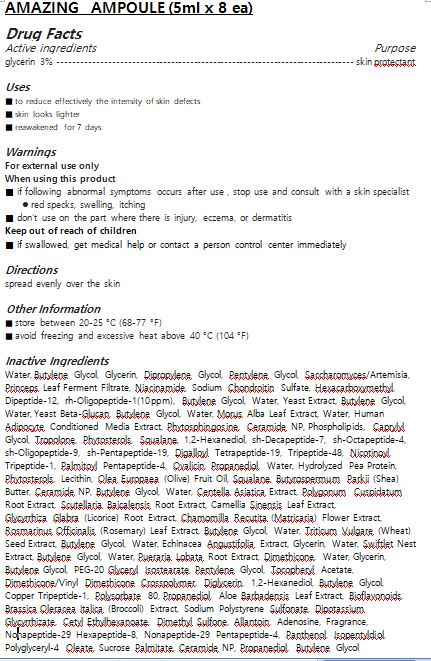 DRUG LABEL: AMAZING AMPOULE
NDC: 72943-0002 | Form: LIQUID
Manufacturer: DAONMEDICOS CO.
Category: otc | Type: HUMAN OTC DRUG LABEL
Date: 20190324

ACTIVE INGREDIENTS: GLYCERIN 3 g/100 mL
INACTIVE INGREDIENTS: WATER; ALLANTOIN

Drug Facts

ACTIVE INGREDIENT

GLYCERIN

INACTIVE INGREDIENT

Water
Butylene Glycol
Glycerin
Dipropylene Glycol
Pentylene Glycol
Saccharomyces/Artemisia Princeps Leaf Ferment Filtrate
Niacinamide
Sodium Chondroitin Sulfate
Hexacarboxymethyl Dipeptide-12
rh-Oligopeptide-1(10ppm)
Butylene Glycol
Water
Yeast Extract
Butylene Glycol
Water
Yeast Beta-Glucan
Butylene Glycol
Water
Morus Alba Leaf Extract
Water
Human Adipocyte Conditioned Media Extract
Phytosphingosine
Ceramide NP
Phospholipids
Caprylyl Glycol
Tropolone
Phytosterols
Squalane
1,2-Hexanediol
sh-Decapeptide-7
sh-Octapeptide-4
sh-Oligopeptide-9
sh-Pentapeptide-19
Digalloyl Tetrapeptide-19
Tripeptide-48
Nicotinoyl Tripeptide-1
Palmitoyl Pentapeptide-4
Ovalicin
Propanediol
Water
Hydrolyzed Pea Protein
Phytosterols
Lecithin
Olea Europaea (Olive) Fruit Oil
Squalane
Butyrospermum Parkii (Shea) Butter
Ceramide NP
Butylene Glycol
Water
Centella Asiatica Extract
Polygonum Cuspidatum Root Extract
Scutellaria Baicalensis Root Extract
Camellia Sinensis Leaf Extract
Glycyrrhiza Glabra (Licorice) Root Extract
Chamomilla Recutita (Matricaria) Flower Extract
Rosmarinus Officinalis (Rosemary) Leaf Extract
Butylene Glycol
Water
Triticum Vulgare (Wheat) Seed Extract
Butylene Glycol
Water
Echinacea Angustifolia Extract
Glycerin
Water
Swiftlet Nest Extract
Butylene Glycol
Water
Pueraria Lobata Root Extract
Dimethicone
Water
Glycerin
Butylene Glycol
PEG-20 Glyceryl Isostearate
Pentylene Glycol
Tocopheryl Acetate
Dimethicone/Vinyl Dimethicone Crosspolymer
Diglycerin
1,2-Hexanediol
Butylene Glycol
Copper Tripeptide-1
Polysorbate 80
Propanediol
Aloe Barbadensis Leaf Extract
Bioflavonoids
Brassica Oleracea Italica (Broccoli) Extract
Sodium Polystyrene Sulfonate
Dipotassium Glycyrrhizate
Cetyl Ethylhexanoate
Dimethyl Sulfone
Allantoin
Adenosine
Fragrance
Nonapeptide-29 Hexapeptide-8
Nonapeptide-29 Pentapeptide-4
Panthenol
Isopentyldiol
Polyglyceryl-4 Oleate
Sucrose Palmitate
Ceramide NP
Propanediol
Butylene Glycol

PURPOSE

■ to reduce effectively the intensity of skin defects

■ skin looks lighter

■ reawakened for 7 days

keep out of reach of the children

INDICATIONS AND USAGE

spread evenly over the skin

WARNINGS

■ if following abnormal symptoms occurs after use , stop use and consult with a skin specialist

red specks, swelling, itching

■ don’t use on the part where there is injury, eczema, or dermatitis

Keep out of reach of children

■ if swallowed, get medical help or contact a person control center immediately

DOSAGE AND ADMINISTRATION

for external use only